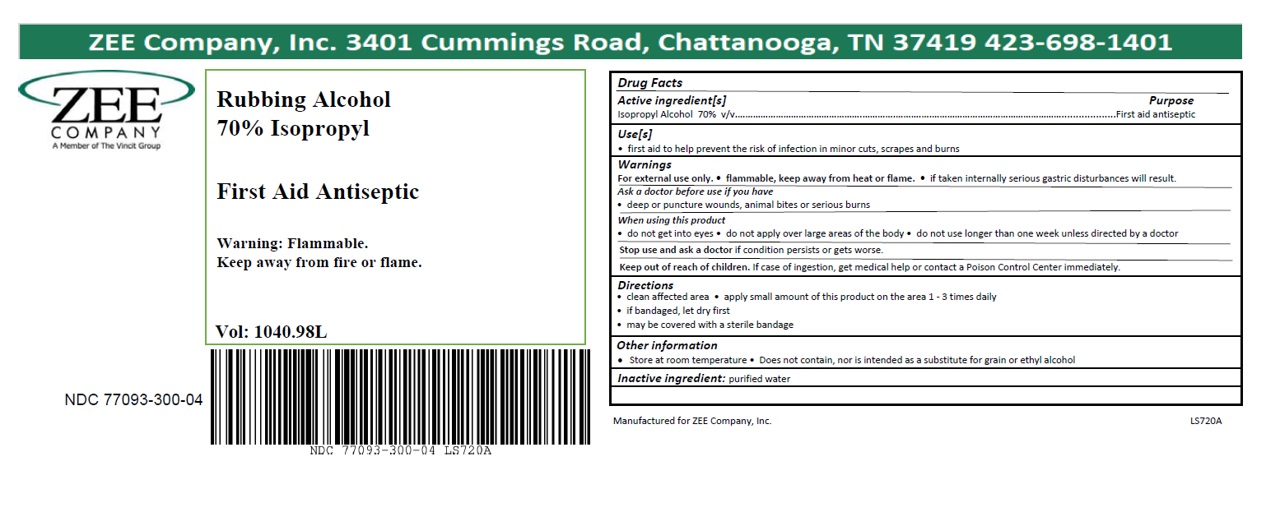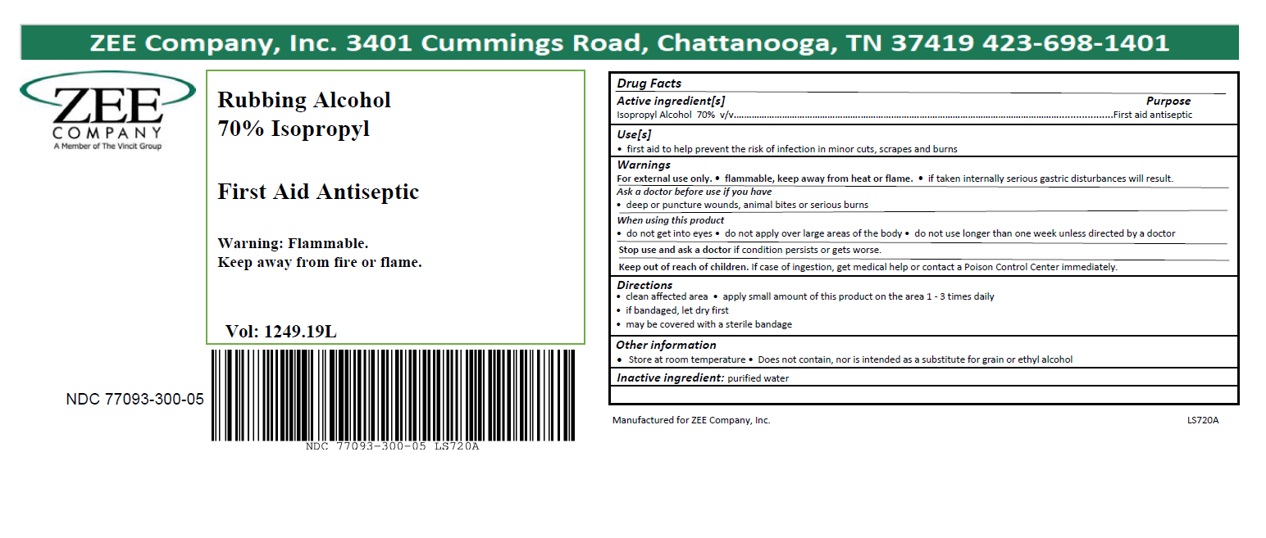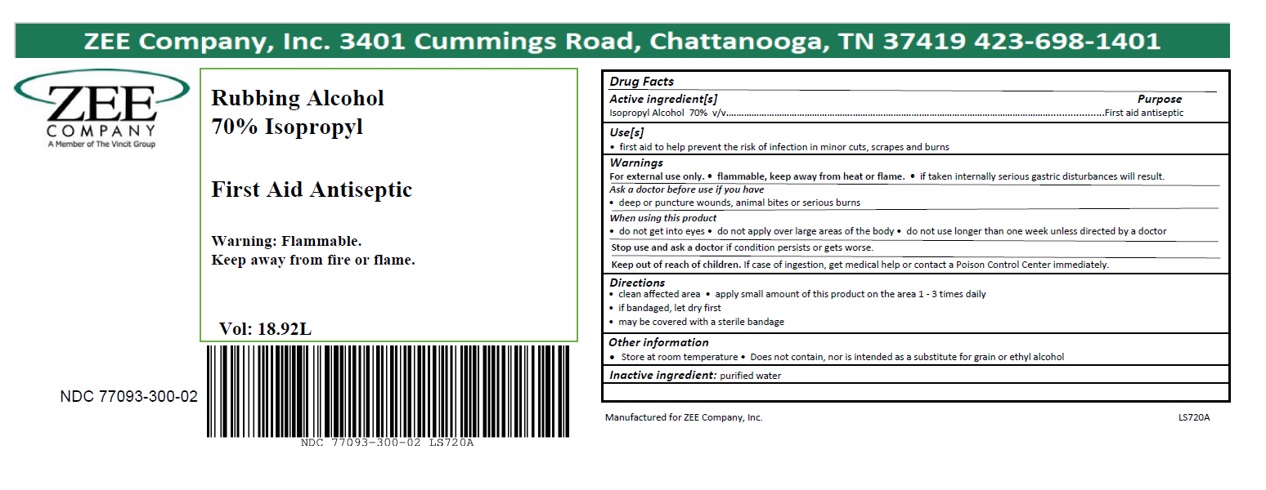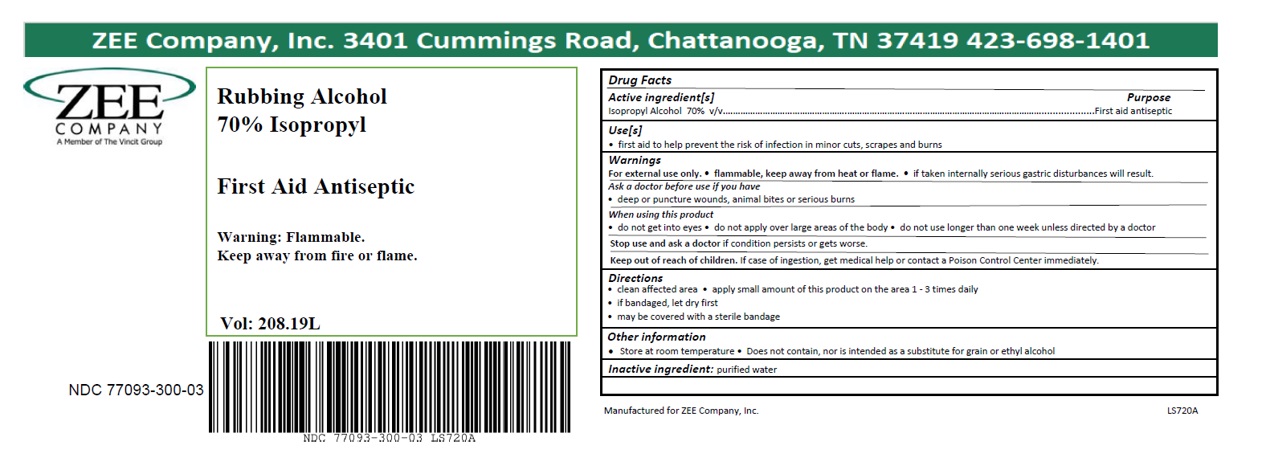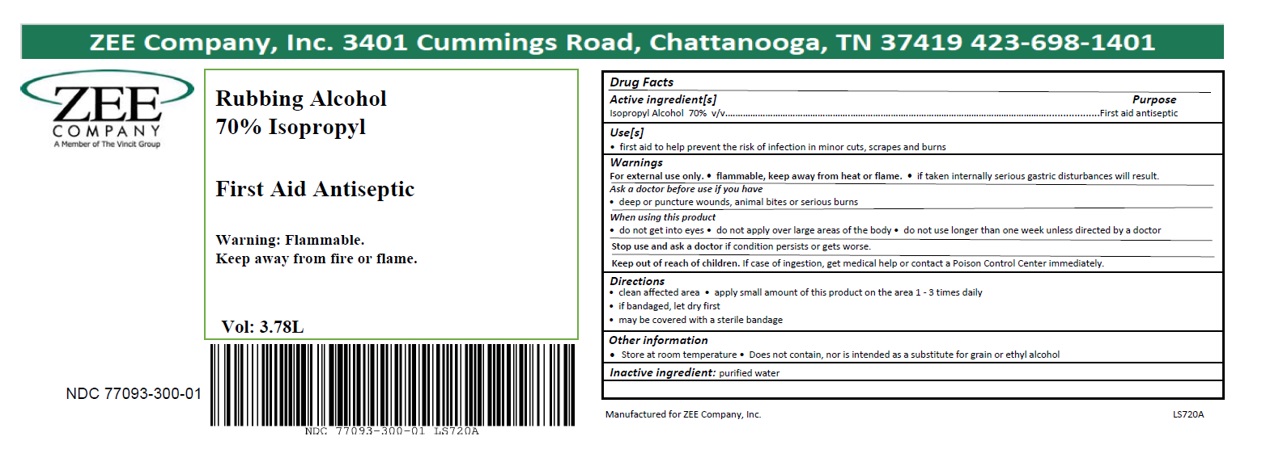 DRUG LABEL: Rubbing Alcohol 70% Isopropyl
NDC: 77093-300 | Form: LIQUID
Manufacturer: Vincit Zee
Category: otc | Type: HUMAN OTC DRUG LABEL
Date: 20210422

ACTIVE INGREDIENTS: ISOPROPYL ALCOHOL 0.7 L/1 L
INACTIVE INGREDIENTS: WATER

Rubbing Alcohol 70% Isopropyl - Cummings Rd.

ACTIVE INGREDIENT

Isopropyl Alcohol 70% v/v

PURPOSE

First aid antiseptic

INDICATIONS AND USAGE

- first aid to help prevent the risk of infection in minor cuts, scrapes and burns

Ask a doctor before use if you have

- deep or puncture wounds, animal bites or serious burns

WARNINGS

- For external use only
- flammable, keep away from heat or flame
- if taken internally serious gastric disturbances will result

Stop use and ask a doctor if condition persists or gets worse

WHEN USING

- do not get into eyes
- do not apply over large areas of the body
- do not use longer than one week unless directed by a doctor

Keep out of reach of children. In case of ingestion, get medical help or contact a Poison Control Center immediately.

DOSAGE AND ADMINISTRATION

- clean affected area
- apply small amount of this product on the area 1-3 times daily
- if bandaged, let dry first
- may be covered with a sterile bandage

STORAGE AND HANDLING

- Store at room temperature
- Does not contain, nor is intended as a substitute for grain or ethyl alcohol

INACTIVE INGREDIENT

purified water

PACKAGE LABEL

3.78L NDC: 77093-300-01

18.92L NDC: 77093-300-02

208.19L NDC: 77093-300-03

1040.98L NDC: 77093-300-04

1249.19L NDC: 77093-300-05